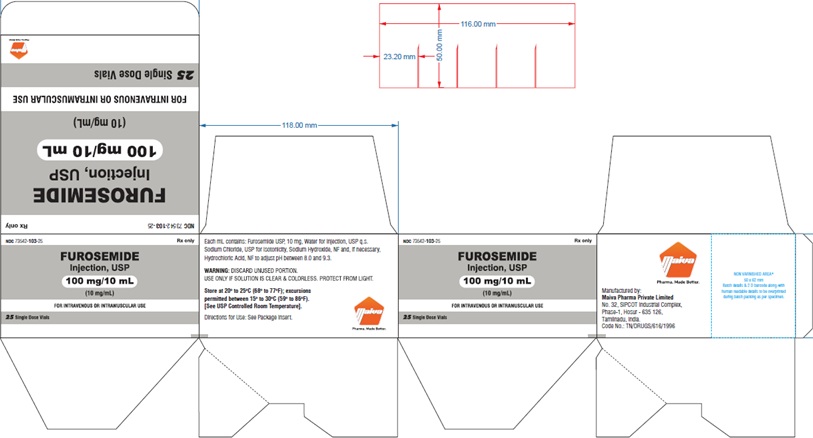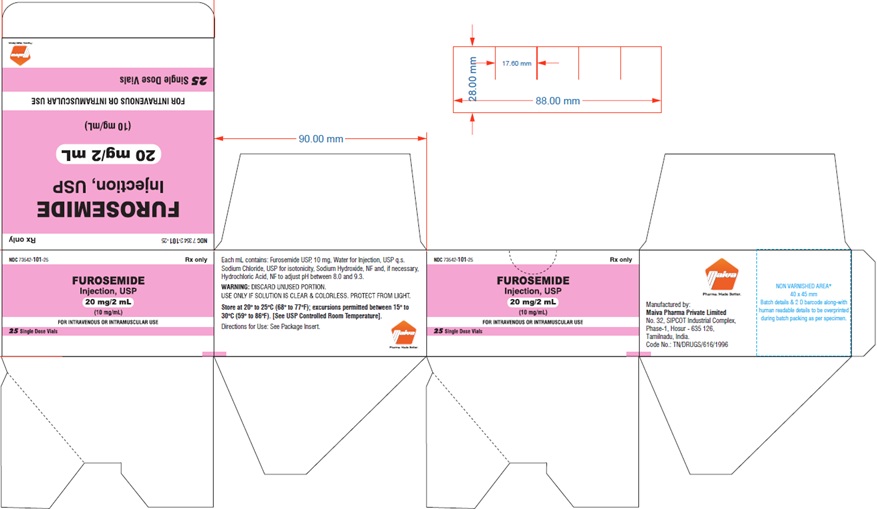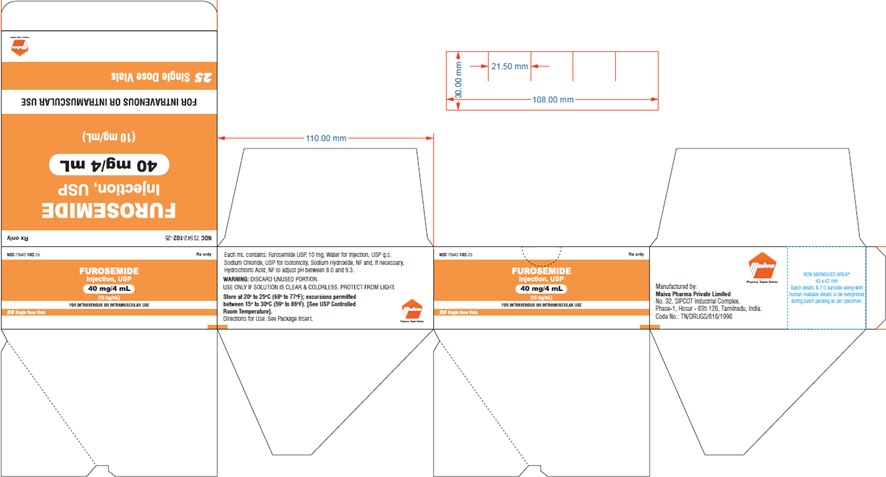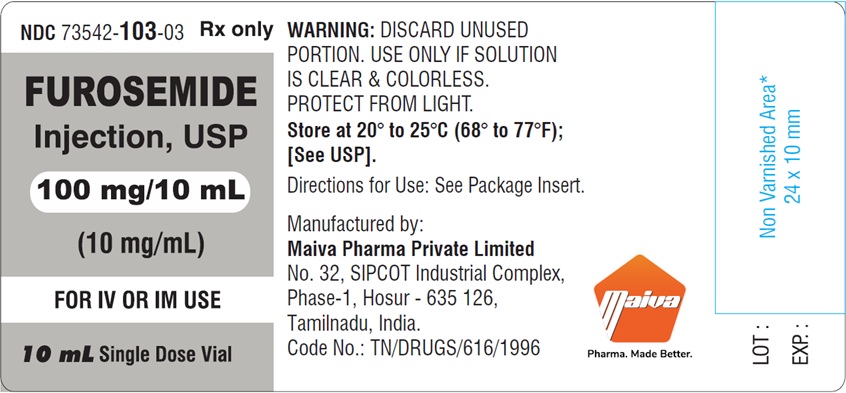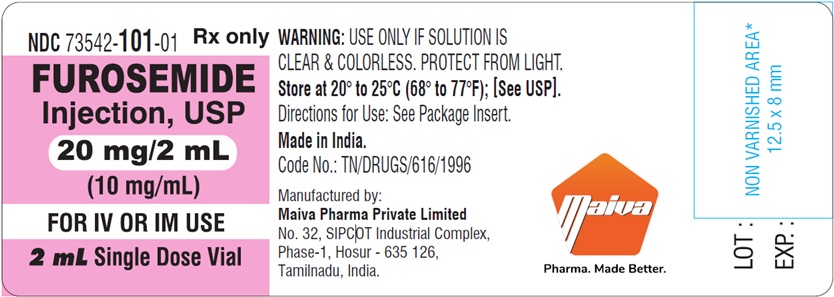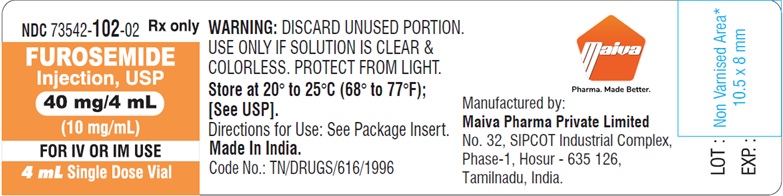 DRUG LABEL: Furosemide
NDC: 73542-101 | Form: INJECTION
Manufacturer: Maiva Pharma Private Limited
Category: prescription | Type: HUMAN PRESCRIPTION DRUG LABEL
Date: 20250613

ACTIVE INGREDIENTS: FUROSEMIDE 10 mg/1 mL
INACTIVE INGREDIENTS: SODIUM CHLORIDE; SODIUM HYDROXIDE; HYDROCHLORIC ACID; WATER

Rx only

WARNINGS

Furosemide is a potent diuretic which, if given in excessive amounts, can lead to a profound diuresis with water and electrolyte depletion. Therefore, careful medical supervision is required and dose and dose schedule must be adjusted to the individual patient's needs. (See DOSAGE AND ADMINISTRATION.)

PACKAGE LABEL.PRINCIPAL DISPLAY PANEL

NDC 73542-101-01
Furosemide Injection, USP
20 mg/2 mL
(10 mglmL)
FOR IV OR IM USE
Rx only
2 mL Single-Dose vial

NDC 73542-101-25
Furosemide Injection, USP
20 mg/2 mL
(10 mglmL)
FOR IV OR IM USE
Rx only
25 Single-Dose vial

PACKAGE LABEL.PRINCIPAL DISPLAY PANEL

NDC 73542-102-02
Furosemide Injection, USP
40 mg/4 mL
(10 mglmL)
FOR IV OR IM USE
Rx only
4 mL Single-Dose vial

NDC 73542-102-25
Furosemide Injection, USP
40 mg/4 mL
(10 mglmL)
FOR IV OR IM USE
Rx only
25 Single-Dose via

PACKAGE LABEL.PRINCIPAL DISPLAY PANEL

NDC 73542-103-03
Furosemide Injection, USP
100 mg/10 mL
(10 mglmL)
FOR IV OR IM USE
Rx only
10 mL Single-Dose vial

NDC 73542-103-25
Furosemide Injection, USP
100 mg/10 mL
(10 mglmL)
FOR IV OR IM USE
Rx only

25 Single-Dose vial